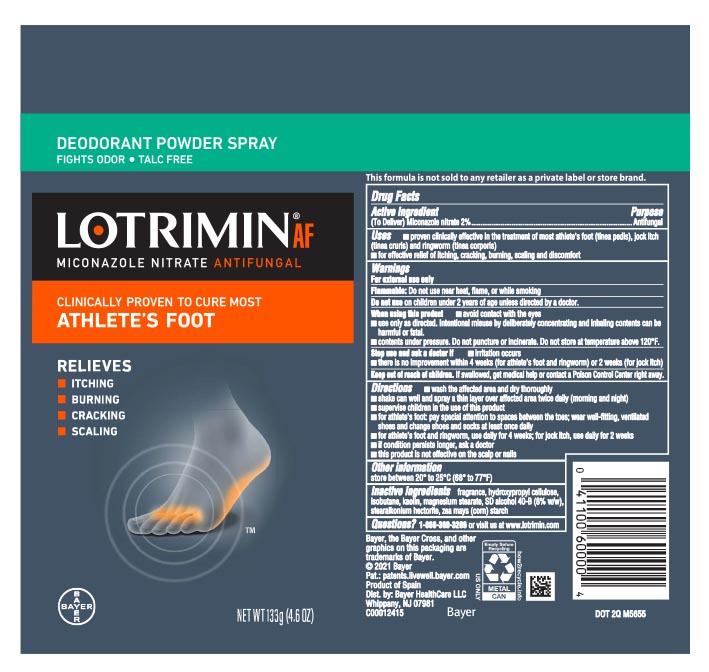 DRUG LABEL: Lotrimin
NDC: 11523-0135 | Form: AEROSOL, POWDER
Manufacturer: Bayer HealthCare LLC.
Category: otc | Type: HUMAN OTC DRUG LABEL
Date: 20251204

ACTIVE INGREDIENTS: MICONAZOLE NITRATE 20 mg/1 g
INACTIVE INGREDIENTS: STEARALKONIUM HECTORITE; HYDROXYPROPYL CELLULOSE, UNSPECIFIED; KAOLIN; ISOBUTANE; MAGNESIUM STEARATE; STARCH, CORN

Lotrimin® AF Deodorant Powder Spray Talc Free

Drug Facts

Active ingredient

Miconazole nitrate 2%

Purpose

Antifungal

Uses

- proven clinically effective in the treatment of most athlete's foot (tinea pedis), jock itch (tinea cruris) and ringworm (tinea corporis)
- for effective relief of itching, cracking, burning, scaling and discomfort

Warnings

For external use only

Flammable

For external use only

flammable: Do not use near heat, flame, or while smoking

Do not use on children under 2 years of age unless directed by a doctor

When using this product

- avoid contact with the eyes
- use only as directed. Intentional misuse by deliberately concentrating and inhaling contents can be harmful or fatal.
- contents under pressure. Do not puncture or incinerate. Do not store at temperature above 120˚F.

Stop use and ask a doctor if

- irritation occurs
- there is no improvement within 4 weeks (for athlete's foot and ringworm) or 2 weeks (for jock itch)

Keep out of reach of children. If swallowed, get medical help or contact a Poison Control Center right away.

Directions

- wash affected area and dry thoroughly
- shake can well and spray a thin layer over affected area twice daily (morning and night)
- supervise children in the use of this product
- for athlete's foot: pay special attention to spaces between the toes; wear well-fitting, ventilated shoes and change shoes and socks at least once daily
- for athlete's foot and ringworm, use daily for 4 weeks; for jock itch, use daily for 2 weeks
- if condition persists longer, ask a doctor
- this product is not effective on the scalp or nails

Other information

store between 20° to 25°C 68° to 77°F

Questions?

1-866-360-3266 or visit us at www.lotrimin.com

Inactive ingredients

Fragrance, hydroxypropyl cellulose, isobutane, kaolin, magnesium stearate, SD alcohol 40-B (8% v/v), stearalkonium hectorite, zea mays (corn) starch

PRINCIPAL DISPLAY PANEL - 133 g Can Label

Deodorant Powder Spray
fights odor . talc free

LOTRIMIN® AF
miconazole nitrate
ANTIFUNGAL

Clinically Proven To Cure
Most Athlete's Foot

Relieves

- Itching
- Burning
- Cracking

& Scaling

NET WT 133g (4.6 OZ)